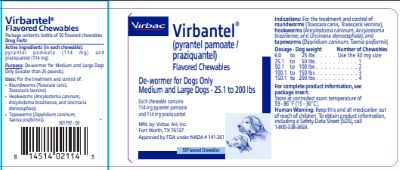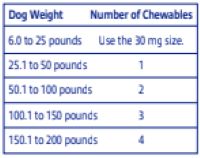 DRUG LABEL: Virbantel
NDC: 51311-741 | Form: TABLET, CHEWABLE
Manufacturer: Virbac AH, Inc
Category: animal | Type: OTC ANIMAL DRUG LABEL
Date: 20260218

ACTIVE INGREDIENTS: PYRANTEL PAMOATE 114 mg/1 1; PRAZIQUANTEL 114 mg/1 1

Virbantel® Flavored Chewables

Package contents:

Bottle of 50 flavored chewables

Drug Facts

Active Ingredients (in each chewable): pyrantel pamoate (114 mg) and praziquantel (114 mg)

Purpose: De-wormer for Medium and Large Dogs Only (Greater than 25 pounds)

Uses: For the treatment and control of:

• Roundworms (Toxocara canis, Toxascaris leonina)
• Hookworms (Ancylostoma caninum, Ancylostoma braziliense, and Uncinaria stenocephala)
• Tapeworms (Dipylidium caninum, Taenia pisiformis)

When Using This Product:

• Consult your veterinarian for assistance in the diagnosis, treatment, and control of parasitism.
• Do not de-worm a dog or puppy that is sick. Consult a veterinarian for diagnosis of the illness.
• VIRBANTEL Flavored Chewables are safe for use in puppies 12 weeks or older and adult dogs. Safety in breeding dogs and pregnant bitches has not been tested.

You May Notice:

Vomiting, loose stools (with or without blood) and decreased activity following treatment. If you notice these signs, contact a veterinarian.

Human Warning:

Keep this and all medication out of the reach of children. To obtain product information, including a Safety Data Sheet (SDS), call 1-800-338-3659.

Directions:

Each flavored chewable contains 114 mg of pyrantel pamoate and 114 mg of praziquantel. The dose for each drug is 2.27 mg per pound of body weight (5 mg/kg). Please refer to the following dosing table for help finding the right dose for your dog.

VIRBANTEL Flavored Chewables Dosing Table

You should weigh your dog to make sure you are giving the right dose.

- VIRBANTEL Flavored Chewables are palatable if offered by hand. If your dog does not voluntarily eat the chewable, you can hide the chewable in a small amount of food or place it in the back of the dog's mouth for forced swallowing.
- Make sure that the dog eats the complete dose.
- Watch your dog for a few minutes after dosing to make sure the chewable is not rejected.

Other Information:

Recommended De-Worming Schedule: Consult your veterinarian for assistance in the diagnosis, treatment, and control of parasitism. De-worming schedules may vary depending on the climate where you live and the activity of your dog.

Re-treatment: Re-treatment of your dog may be necessary as determined by laboratory fecal examination and/or if your dog is living where re-infections are likely to occur. Consult your veterinarian for assistance in the diagnosis and prevention of re-infection. In case of re-infection with tapeworms (Dipylidium caninum), consult your veterinarian for advice on how to remove fleas from the dog and the environment.

Manufactured by:

Virbac AH, Inc.
Fort Worth, TX 76137

Storage:

Store at controlled room temperature of 59-86˚F (15-30˚C).

Questions? Comments?

To report a suspected adverse reaction, call
1-800-338-3659.

2/2019 301799-03
Approved by FDA under NADA # 141-261

© 2019 Virbac Corporation. All Rights Reserved.

VIRBANTEL is a registered trademark of Virbac S.A.